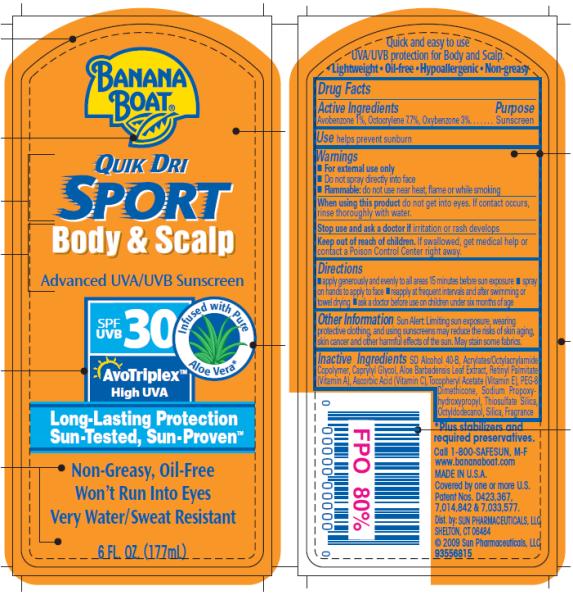 DRUG LABEL: Banana Boat Quik Dri Sport Body and Scalp SPF 30
NDC: 17630-2028 | Form: LOTION
Manufacturer: Accra-Pac, Inc.
Category: otc | Type: HUMAN OTC DRUG LABEL
Date: 20100327

ACTIVE INGREDIENTS: AVOBENZONE 0.01 mL/1 mL; OCTOCRYLENE 0.077 mL/1 mL; OXYBENZONE 0.03 mL/1 mL
INACTIVE INGREDIENTS: CAPRYLYL GLYCOL; ALOE VERA LEAF; VITAMIN A PALMITATE; ASCORBIC ACID; .ALPHA.-TOCOPHEROL ACETATE, D-; OCTYLDODECANOL; SILICON DIOXIDE

Banana Boat Quik Dri Sport Body and Scalp SPF 30

Drug Facts

Active Ingredients

Avobenzone 0.01mL / 1mL

Octocrylene 0.077mL / 1mL

Oxybenzone 0.03mL / 1mL

Purpose

Sunscreen

Use

helps prevent sunburn

Warnings

- For external use only
- Do not spray directly into face
- Flammable: do not use near heat, flame or while smoking

When using this product

do not get into eyes. If contact occurs, rinse thoroughly with water.

Stop use and ask a doctor if

irritation or rash develops

Keep out of reach of children.

If swallowed, get medical help or contact a Poison Control Center right away.

Directions

- apply generously and evenly to all areas 15 minutes before sun exposure
- spray on hands to apply to face
- reapply at frequent intervals and after swimming or towel drying
- ask a doctor before use on children under six months of age

Other Information

Sun Alert: Limiting sun exposure, wearing protective clothing, and using sunscreens may reduce the risks of skin aging, skin cancer and other harmful effects of the sun. May stain some fabrics.

Inactive Ingredients

SD Alcohol 40-B, Acrylates/Octylacrylamide Copolymer, Caprylyl Glycol, Aloe Barbadensis Leaf Extract, Retinyl Palmitate (Vitamin A), Ascorbic Acid (Vitamin C), Tocopheryl Acetate (Vitamin E), PEG-8 Dimethicone, Sodium Propoxyhydroxypropyl, Thiosulfate Silica, Octyldodecanol, Silica, Fragrance

Call 1-800-SAFESUN, M-F
Dist. by: SUN PHARMACEUTICALS, LLC

PRINCIPAL DISPLAY PANEL

BANANA
BOAT®
QUIK DRI
SPORT
Body & Scalp
Advanced UVA/UVB Sunscreen
SPF/UVB 30 Infused with Pure Aloe Vera*
AvoTriplex TM
High UVA
Long-Lasting Protection
Sun-Tested, Sun-Proven TM
Non-Greasy, Oil-Free
Won’t Run Into Eyes
Very Water/Sweat Resistant
6 FL. OZ. (177mL)